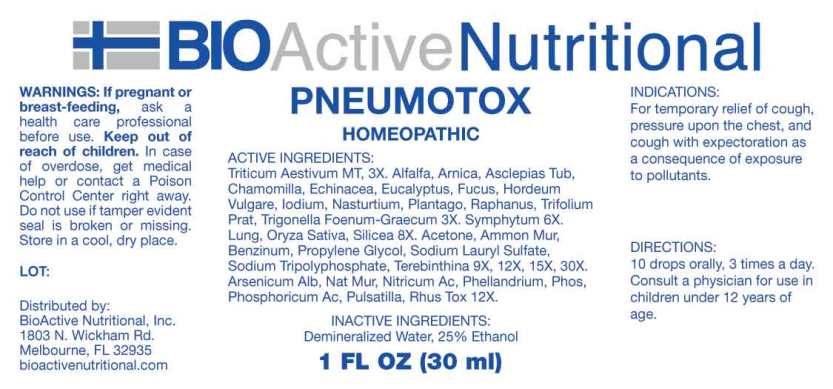 DRUG LABEL: Pneumotox
NDC: 43857-0533 | Form: LIQUID
Manufacturer: BioActive Nutritional, Inc.
Category: homeopathic | Type: HUMAN OTC DRUG LABEL
Date: 20230712

ACTIVE INGREDIENTS: TRITICUM AESTIVUM WHOLE 1 [hp_X]/1 mL; ALFALFA 3 [hp_X]/1 mL; ARNICA MONTANA 3 [hp_X]/1 mL; ASCLEPIAS TUBEROSA ROOT 3 [hp_X]/1 mL; MATRICARIA RECUTITA 3 [hp_X]/1 mL; ECHINACEA ANGUSTIFOLIA WHOLE 3 [hp_X]/1 mL; EUCALYPTUS GLOBULUS LEAF 3 [hp_X]/1 mL; FUCUS VESICULOSUS 3 [hp_X]/1 mL; HORDEUM VULGARE TOP 3 [hp_X]/1 mL; IODINE 3 [hp_X]/1 mL; NASTURTIUM OFFICINALE 3 [hp_X]/1 mL; PLANTAGO MAJOR 3 [hp_X]/1 mL; DAIKON 3 [hp_X]/1 mL; TRIFOLIUM PRATENSE FLOWER 3 [hp_X]/1 mL; TRIGONELLA FOENUM-GRAECUM WHOLE 3 [hp_X]/1 mL; SYMPHYTUM OFFICINALE WHOLE 6 [hp_X]/1 mL; SUS SCROFA LUNG 8 [hp_X]/1 mL; ORYZA SATIVA WHOLE 8 [hp_X]/1 mL; SILICON DIOXIDE 8 [hp_X]/1 mL; ACETONE 9 [hp_X]/1 mL; SODIUM TRIPOLYPHOSPHATE 9 [hp_X]/1 mL; PROPYLENE GLYCOL 9 [hp_X]/1 mL; BENZENE 9 [hp_X]/1 mL; AMMONIUM CHLORIDE 9 [hp_X]/1 mL; SODIUM LAURYL SULFATE 9 [hp_X]/1 mL; TURPENTINE OIL 9 [hp_X]/1 mL; ARSENIC TRIOXIDE 12 [hp_X]/1 mL; SODIUM CHLORIDE 12 [hp_X]/1 mL; NITRIC ACID 12 [hp_X]/1 mL; OENANTHE AQUATICA FRUIT 12 [hp_X]/1 mL; PHOSPHORIC ACID 12 [hp_X]/1 mL; PHOSPHORUS 12 [hp_X]/1 mL; PULSATILLA PRATENSIS WHOLE 12 [hp_X]/1 mL; TOXICODENDRON PUBESCENS LEAF 12 [hp_X]/1 mL
INACTIVE INGREDIENTS: WATER; ALCOHOL

Drug Facts:

ACTIVE INGREDIENTS:

Triticum Aestivum 1X, 3X Alfalfa 3X, Arnica Montana 3X, Asclepias Tuberosa 3X, Chamomilla 3X, Echinacea (Angustifolia) 3X, Eucalyptus Globulus 3X, Fucus Vesiculosus 3X, Hordeum Vulgare 3X, Iodium 3X, Nasturtium Aquaticum 3X, Plantago Major 3X, Raphanus Sativus 3X, Trifolium Pratense 3X, Trigonella Foenum-Graecum 3X, Symphytum Officinale 6X, Lung (Suis) 8X, Oryza Sativa 8X, Silicea 8X, Acetone 9X, 12X, 15X, 30X, Sodium Tripolyphosphate 9X, 12X, 15X, 30X, Propylene Glycol 9X, 12X, 15X, 30X, Benzinum 9X, 12X, 15X, 30X, Ammonium Muriaticum 9X, 12X, 15X, 30X, Sodium Lauryl Sulfate 9X, 12X, 15X, 30X, Terebinthina 9X, 12X, 15X, 30X, Arsenicum Album 12X, Natrum Muriaticum 12X, Nitricum Acidum 12X, Phellandrium Aquaticum 12X, Phosphoricum Acidum 12X, Phosphorus 12X, Pulsatilla (Pratensis) 12X, Rhus Tox 12X.

INDICATIONS:

For temporary relief of cough, pressure upon the chest, and cough with expectoration as a consequence of exposure to pollutants.

WARNINGS:

If pregnant or breast-feeding, ask a health care professional before use.

Keep out of reach of children. In case of overdose, get medical help or contact a Poison Control Center right away.

Do not use if tamper evident seal is broken or missing.

Store in cool, dry place.

Keep out of reach of children. In case of overdose, get medical help or contact a Poison Control Center right away.

DIRECTIONS:

10 drops orally, 3 times a day. Consult a physician for use in children under 12 years of age.

INDICATIONS:

For temporary relief of cough, pressure upon the chest, and cough with expectoration as a consequence of exposure to pollutants.

INACTIVE INGREDIENTS:

Demineralized Water, 25% Ethanol

QUESTIONS:

Distributed by:
BioActive Nutritional, Inc.
1803 N. Wickham Rd.
Melbourne, FL 32935
bioactivenutritional.com

*For a complete list of Environmental Isodes contact BioActive Nutritional, Inc.

PACKAGE LABEL DISPLAY:

BIOActive Nutritional
PNEUMOTOX
HOMEOPATHIC
1 FL OZ (30 ml)